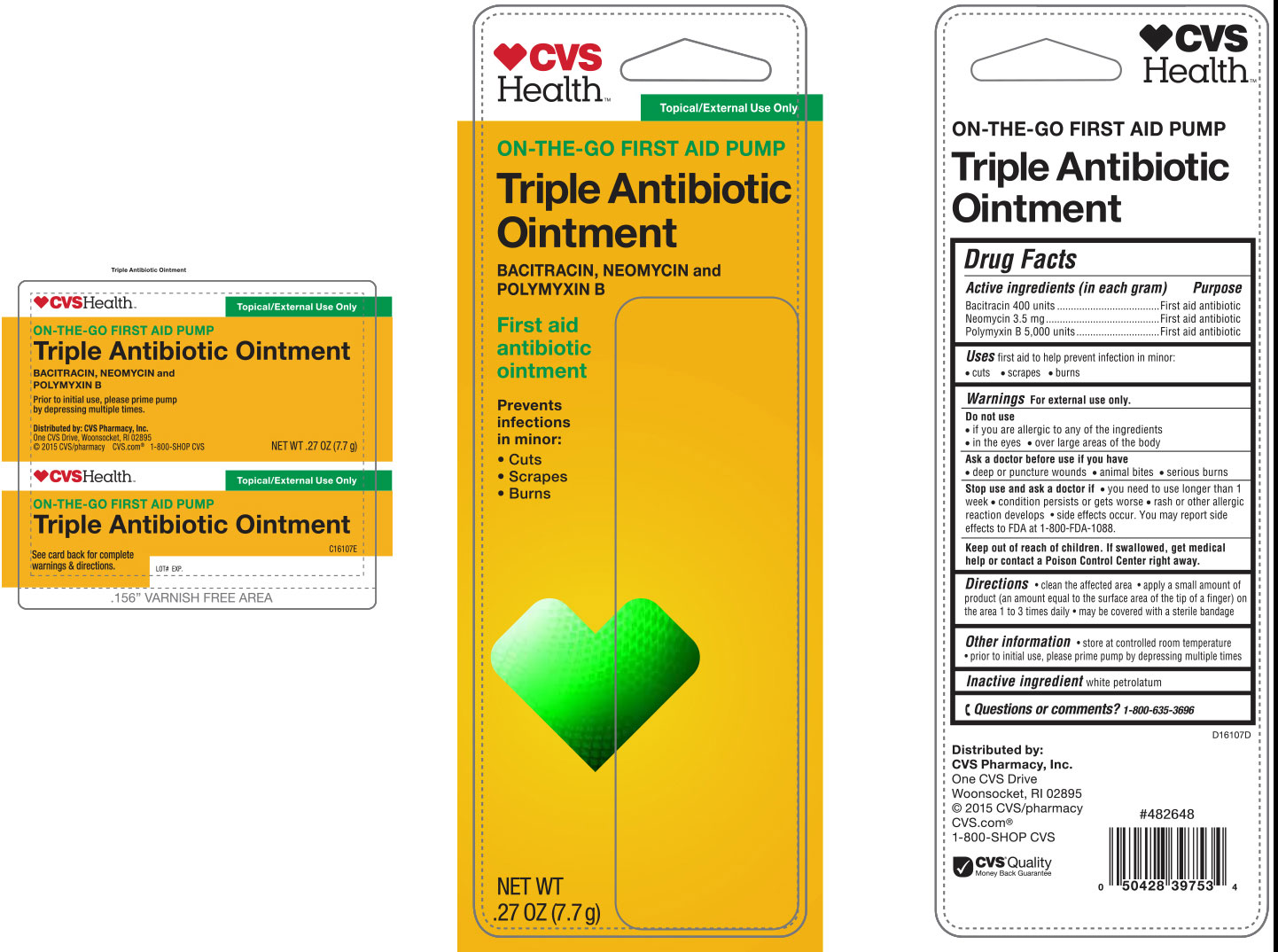 DRUG LABEL: CVS Triple Antibiotic
NDC: 69842-610 | Form: OINTMENT
Manufacturer: CVS Pharmacy
Category: otc | Type: HUMAN OTC DRUG LABEL
Date: 20170104

ACTIVE INGREDIENTS: BACITRACIN ZINC 400 [USP'U]/1 g; NEOMYCIN SULFATE 3.5 mg/1 g; POLYMYXIN B SULFATE 5000 [USP'U]/1 g
INACTIVE INGREDIENTS: PETROLATUM

Package Labeling

Drug Facts

Active Ingredients (in each gram)

Bacitracin 400 units

Neomycin 3.5 mg

Polymyxin B 5,000 units

Uses

first aid to help prevent infection in minor:
• cuts • scrapes • burns

Warnings

For external use only.

Do not use

• if you are allergic to any of the ingredients
• in the eyes
• over large areas of the body

Ask a doctor before use if you have

• deep or puncture wounds • animal bites • serious burns

Stop use and ask a doctor if

• you need to use longer than 1 week
• condition persists or gets worse
• rash or other allergic reaction develops • side effects occur. You may report side effects to FDA at 1-800-FDA-1088.

Keep out of reach of children. If swallowed, get medical help or contact a Poison Control Center right away.

Directions

• clean the affected area • apply a small amount of product (an amount equal to the surface area of the tip of a finger) on the area 1 to 3 times daily • may be covered with a sterile bandage

Inactive Ingredients

white petrolatum

Purpose

First Aid Antibiotic

Other information

•store at controlled room temperature

• prior to initial use, please prime pump by depressing multiple times

Questions or Comments?

1-800-635-3696